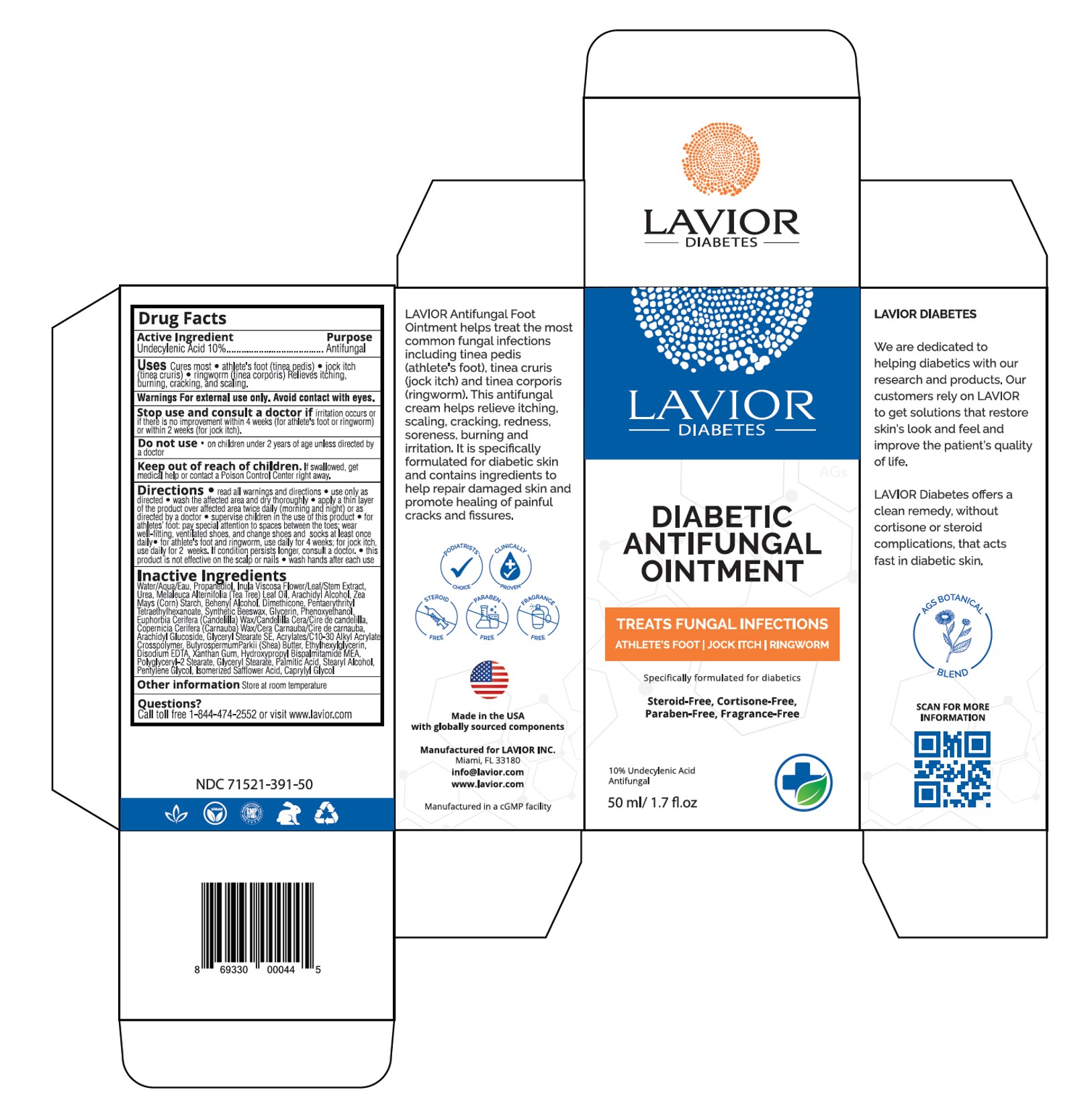 DRUG LABEL: Diabetic Antifungal
NDC: 71521-391 | Form: CREAM
Manufacturer: Lavior Inc
Category: otc | Type: HUMAN OTC DRUG LABEL
Date: 20210509

ACTIVE INGREDIENTS: UNDECYLENIC ACID 10 g/100 g
INACTIVE INGREDIENTS: ARACHIDYL GLUCOSIDE; PROPANEDIOL; PALMITIC ACID; CARBOMER INTERPOLYMER TYPE A (55000 CPS); STARCH, CORN; PENTAERYTHRITYL TETRAETHYLHEXANOATE; UREA; CANDELILLA WAX; PHENOXYETHANOL; PENTYLENE GLYCOL; DOCOSANOL; DIMETHICONE; SYNTHETIC BEESWAX; GLYCERIN; STEARYL ALCOHOL; ARACHIDYL ALCOHOL; DITTRICHIA VISCOSA WHOLE; SHEA BUTTER; ETHYLHEXYLGLYCERIN; XANTHAN GUM; GLYCERYL MONOSTEARATE; TEA TREE OIL; EDETATE DISODIUM; HYDROXYPROPYL BISPALMITAMIDE MONOETHANOLAMIDE; ISOMERIZED SAFFLOWER ACID; CAPRYLYL GLYCOL; CARNAUBA WAX; GLYCERYL STEARATE SE

Active Ingredient

Undecylenic Acid 10%...................Antifungal

Purpose

Antifungal

Uses

Cures most

- athlete's foot (tinea pedis)
- jock itch (tinea cruris)
- ringworm (tinea corporis)

Relieves itching, burning, cracking, and scaling.

Warnings

For external use only. Avoid contact with eyes.

Do not use

on children under 2 years of age unless directed by a doctor

Stop use and consult a doctor if

irritation occurs or if there is no improvement within 4 weeks (for athlete's foot or ringworm) or within 2 weeks (for jock itch).

Keep out of reach of children.

If swallowed, get medical help or contact a Poison Control Center right away.

Directions

- read all warnings and directions
- use only as directed
- wash the affected area and dry thoroughly
- apply a thin layer of the product over affected area twice daily (morning and night) or as directed by a doctor
- Supervise children in the use of this product
- for athletes’ foot: pay special attention to spaces between the toes; wear well-fitting, ventilated shoes, and change shoes and socks at least once daily
- for athlete's foot and ringworm, use daily for 4 weeks; for jock itch, use daily for 2 weeks. If condition persists longer, consult a doctor.
- this product is not effective on the scalp or nails
- wash hands after each use

Other Information

store at room temperature

Inactive ingredients

Water/Aqua/Eau, Propanediol, Inula Viscosa Flower/Leaf/Stem Extract, Urea, Melaleuca Alternifolia (Tea Tree) Leaf Oil, Arachidyl Alcohol, Zea Mays (Corn) Starch, Behenyl Alcohol, Dimethicone, Pentaerythrityl Tetraethylhexanoate, Synthetic Beeswax, Glycerin, Phenoxyethanol, Euphorbia Cerifera (Candelilla) Wax/Candelilla Cera/Cire de Candelilla, Copernicia Cerifera (Carnauba) Wax/Cera Carnauba/Cire de Carnauba, Arachidyl Glucoside, Glyceryl Stearate SE, Acrylates/C10-30 Alkyl Acrylate Crosspolymer, ButyrospermumParkii (Shea) Butter, Ethylhexylglycerin, Disodium EDTA, Xanthan Gum, Hydroxypropyl Bispalmitamide MEA, Polyglyceryl-2 Stearate, Glyceryl Stearate, Palmitic Acid, Stearyl Alcohol, Pentylene Glycol, Isomerized Safflower Acid, Caprylyl Glycol

Questions?

Call toll free 1-844-474-2552 or visit www.lavior.com